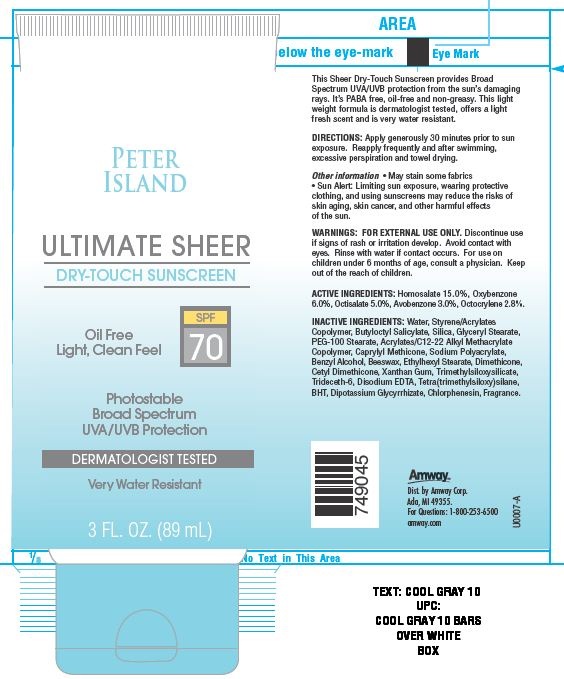 DRUG LABEL: Peter Island Ultimate Sheer Dry Touch Sunscreen
NDC: 10056-707 | Form: LOTION
Manufacturer: Access Business Group LLC
Category: otc | Type: HUMAN OTC DRUG LABEL
Date: 20130628

ACTIVE INGREDIENTS: HOMOSALATE 15 g/100 g; OXYBENZONE 6 g/100 g; AVOBENZONE 3 g/100 g; OCTISALATE 5 g/100 g; OCTOCRYLENE 2.8 g/100 g
INACTIVE INGREDIENTS: WATER; BUTYLOCTYL SALICYLATE; SILICON DIOXIDE; GLYCERYL MONOSTEARATE; PEG-100 STEARATE; CAPRYLYL TRISILOXANE; BENZYL ALCOHOL; YELLOW WAX; ETHYLHEXYL STEARATE; DIMETHICONE; XANTHAN GUM; TRIDECETH-6; EDETATE DISODIUM; TETRASILANE; BUTYLATED HYDROXYTOLUENE; GLYCYRRHIZINATE DIPOTASSIUM; CHLORPHENESIN

ACTIVE INGREDIENTS:

Homosalate 15.0%

Oxybenzone 6.0%

Octisalate 5.0%

Avobenzone 3.0%

Octocrylene 2.8%

WARNINGS:

FOR EXTERNAL USE ONLY.
Avoid contact with eyes. Rinse with water if contact occurs.

STOP USE

Discontinue use if signs of rash or irritation develop.

ASK DOCTOR

For use on children under the age of 6 months consult a physician.

Keep out of reach of children.

DIRECTIONS:

Apply generously and evenly 30 minutes before sun exposure. Reapply frequently and after swimming, excessive perspiration and towel drying.

Other Information

- May stain some fabrics
- Sun Alert: Limiting sun exposure, wearing protective clothing, and using sunscreens may reduce the risks of skin aging, skin cancer, and other harmful effects of the sun.

This Sheer Dry-Touch Sunscreen provides Broad Spectrum UVA/UVB protection from the sun's damaging rays. It's PABA free,oil-free and non-greasy. This light weight formula is dermatologist tested, offers a light fresh scent and is very water resistant.

Principal Display Panel

PETER ISLAND

ULTIMATE SHEER

DRY-TOUCH SUNSCREEN

Oil Free Light, Clean Feel

spf 70

Photostable

Broad Spectrum

UVA/UVB Protection

DERMATOLOGIST TESTED

Very Water Resistant

3 FL.OZ. (89 mL)

INACTIVE INGREDIENTS:

Water, Styrene/Acrylates Copolymer, Butyloctyl Salicylate, Glyceryl Stearate, Silica, PEG-100 Stearate, Acrylates/C12-22 Alkyl Methacrylate Copolymer, Caprylyl Methicone, Sodium Polyacrylate, Benzyl Alcohol, Beeswax, Ethylhexyl Stearate, Dimethicone, Cetyl Dimethicone, Xanthan Gum, Trimethylsiloxysilicate, Trideceth-6, Disodium EDTA, Dipotassium Glycyrrhizate, BHT, Chlorphenesin, Fragrance.